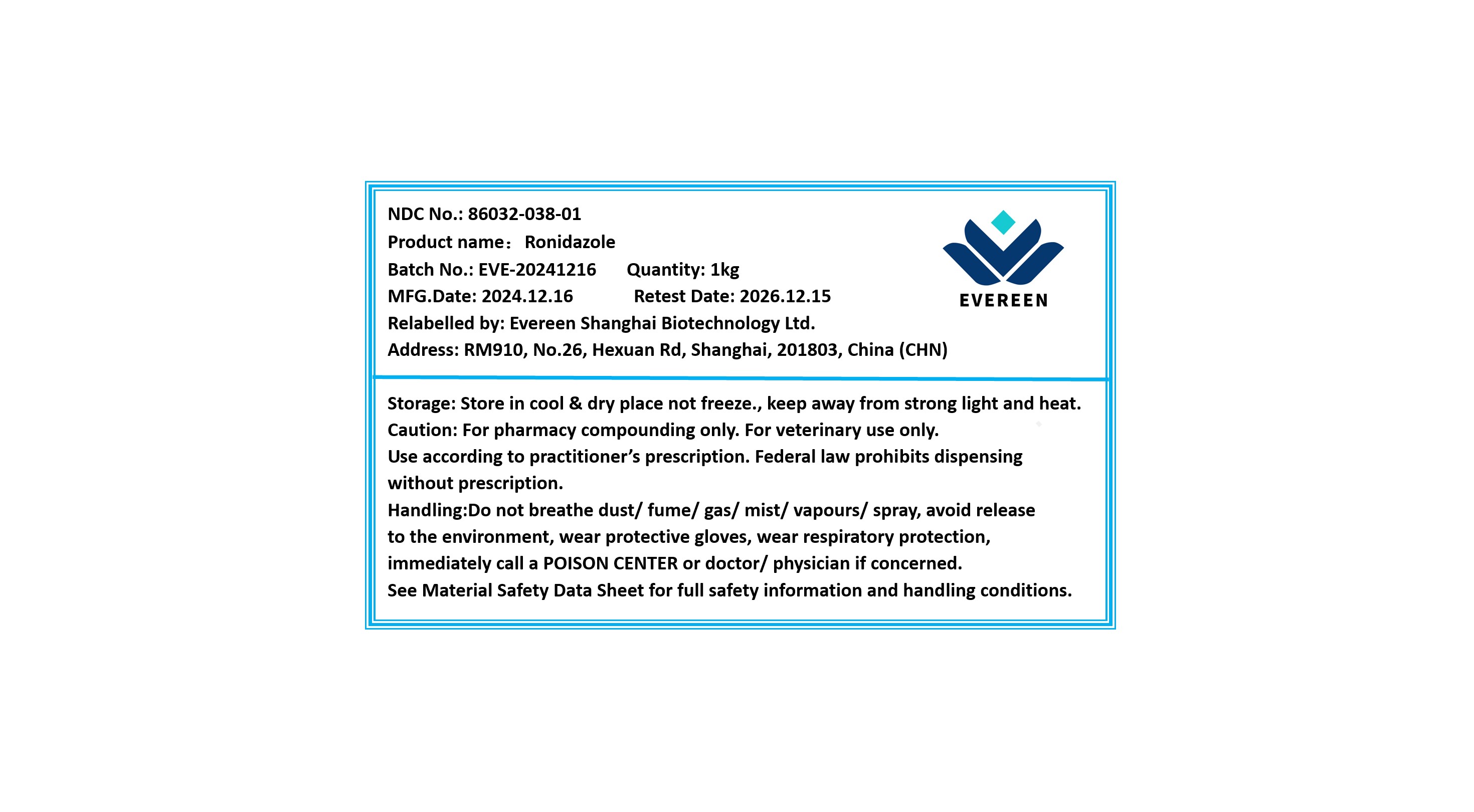 DRUG LABEL: Ronidazole
NDC: 86032-038 | Form: POWDER
Manufacturer: Evereen Shanghai Biotechnology Ltd.
Category: other | Type: BULK INGREDIENT - ANIMAL DRUG
Date: 20250305

ACTIVE INGREDIENTS: RONIDAZOLE 1 kg/1 kg

Ronidazole